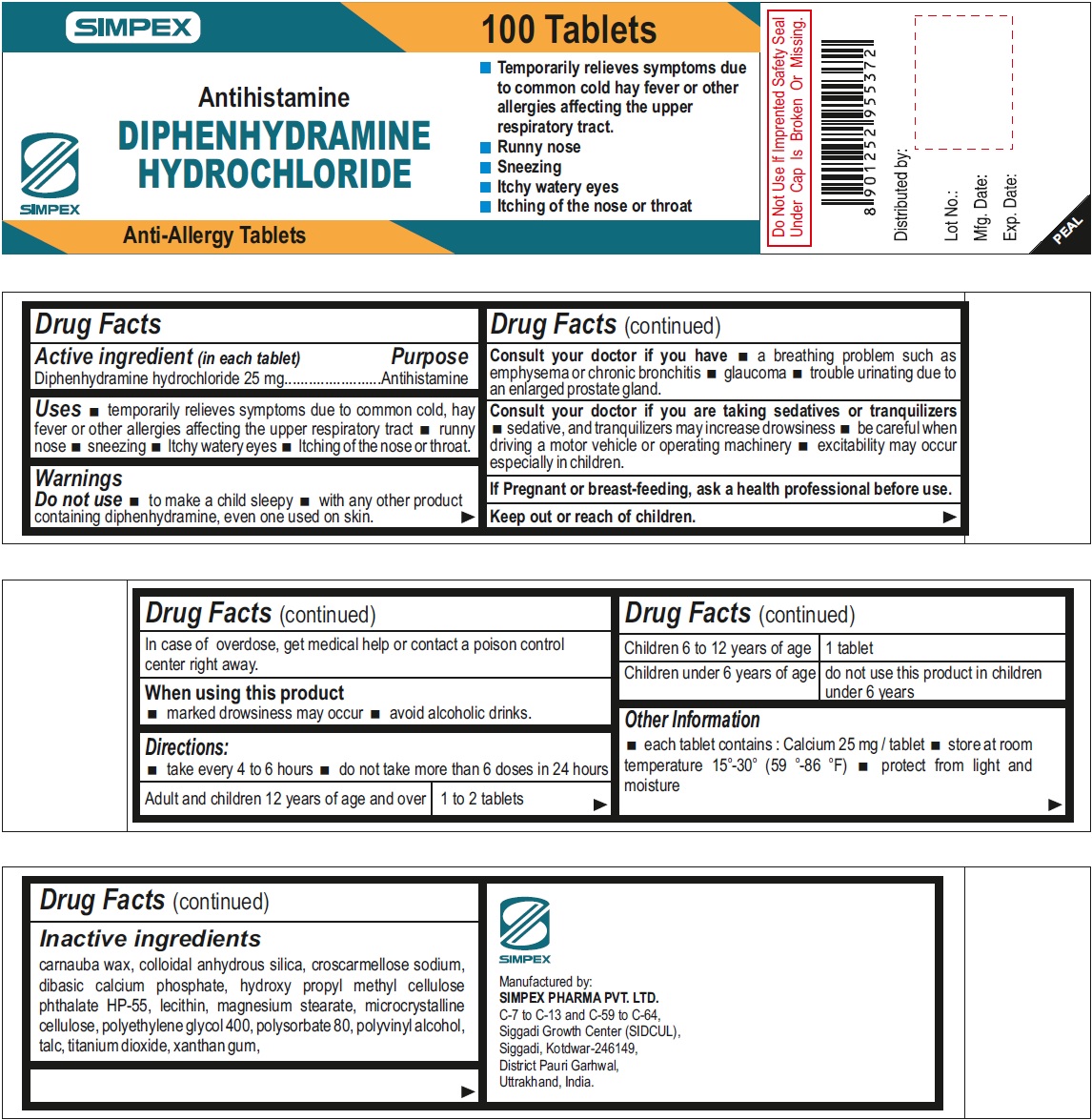 DRUG LABEL: diphenhydramine hydrochloride
NDC: 76457-002 | Form: TABLET
Manufacturer: Simpex Pharma Pvt. Ltd
Category: otc | Type: HUMAN OTC DRUG LABEL
Date: 20231129

ACTIVE INGREDIENTS: DIPHENHYDRAMINE HYDROCHLORIDE 25 mg/1 1
INACTIVE INGREDIENTS: POLYETHYLENE GLYCOL 400; POLYSORBATE 80; POLYVINYL ALCOHOL, UNSPECIFIED; TALC; TITANIUM DIOXIDE; XANTHAN GUM; CARNAUBA WAX; SILICON DIOXIDE; CROSCARMELLOSE SODIUM; ANHYDROUS DIBASIC CALCIUM PHOSPHATE; MAGNESIUM STEARATE; MICROCRYSTALLINE CELLULOSE

Diphenhydramine hydrochloride

Active ingredient (in each tablet)

Diphenhydramine hydrochloride 25 mg

Purpose

Antihistamine

Uses

temporarily relieves symptoms due to common cold, hay fever or other allergies affecting the upper respiratory tract

- runny nose
- sneezing
- Itchy watery eyes
- Itching of the nose or throat.

Warnings

Do not use

- to make a child sleepy
- with any other product containing diphenhydramine, even one used on skin.

Consult your doctor if you have

- a breathing problem such as emphysema or chronic bronchitis
- glaucoma
- trouble urinating due to an enlarged prostate gland.

Consult your doctor if you are taking sedatives or tranquilizers

- sedative, and tranquilizers may increase drowsiness
- be careful when driving a motor vehicle or operating machinery
- excitability may occur especially in children.

If Pregnant or breast-feeding,

ask a health professional before use.

Keep out or reach of children.

In case of overdose, get medical help or contact a poison control center right away.

When using this product

- marked drowsiness may occur
- avoid alcoholic drinks.

Directions:

- take every 4 to 6 hours
- do not take more than 6 does in 24 hours
- Adult and children 12 years of age and over - 1 to 2 tablet
- Children 6 to 12 years of age - 1 tablet
- Children 6 years of age - do not use this product in children under 6 years

Other Information

- each tablet contains: Calcium 25 mg/tablet
- store at room temperature 15°-30° (59°-86° F)
- protect from light and moisture

Inactive ingredient

carnauba wax, colloidal anhydrous silica, croscarmellose sodium, dibasic calcium phosphate, hydroxy propyl methyl cellulose phthalate HP-55, lecithin, magnesium stearate, microcrystalline cellulose, polyethylene glycol 400, polysorbate 80, polyvinyl alcohol, talc, titanium dioxide, xanthan gum,